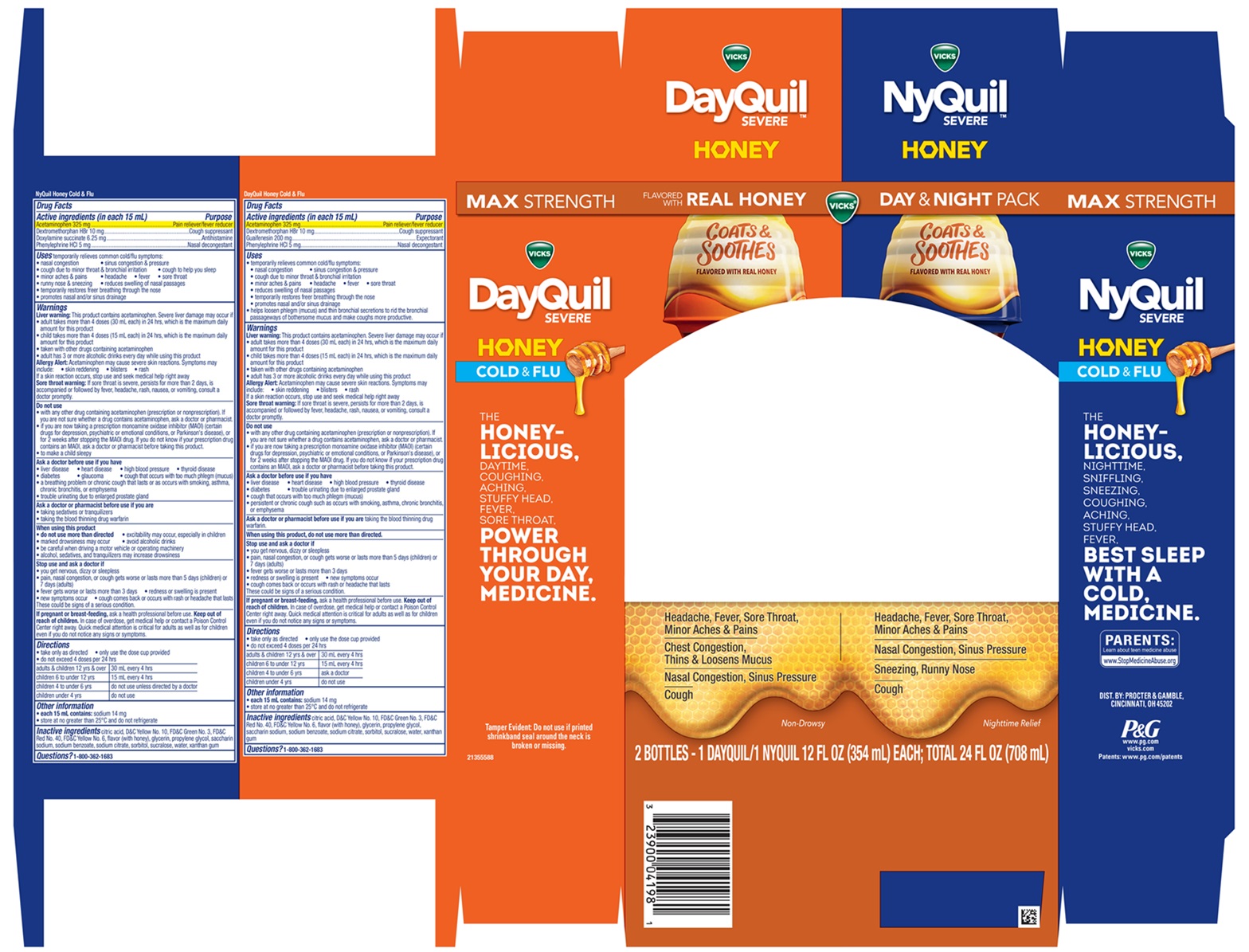 DRUG LABEL: VICKS DayQuil NyQuil SEVERE HONEY
NDC: 84126-326 | Form: KIT | Route: ORAL
Manufacturer: The Procter & Gamble Manufacturing Company
Category: otc | Type: HUMAN OTC DRUG LABEL
Date: 20260219

ACTIVE INGREDIENTS: ACETAMINOPHEN 325 mg/15 mL; GUAIFENESIN 200 mg/15 mL; DEXTROMETHORPHAN HYDROBROMIDE 10 mg/15 mL; PHENYLEPHRINE HYDROCHLORIDE 5 mg/15 mL; ACETAMINOPHEN 325 mg/15 mL; DOXYLAMINE SUCCINATE 6.25 mg/15 mL; DEXTROMETHORPHAN HYDROBROMIDE 10 mg/15 mL; PHENYLEPHRINE HYDROCHLORIDE 5 mg/15 mL
INACTIVE INGREDIENTS: PROPYLENE GLYCOL; CITRIC ACID MONOHYDRATE; D&C YELLOW NO. 10; XANTHAN GUM; FD&C YELLOW NO. 6; SODIUM CITRATE; SUCRALOSE; GLYCERIN; SACCHARIN SODIUM; FD&C GREEN NO. 3; SORBITOL; WATER; SODIUM BENZOATE; FD&C RED NO. 40; FD&C YELLOW NO. 6; GLYCERIN; PROPYLENE GLYCOL; WATER; FD&C RED NO. 40; XANTHAN GUM; D&C YELLOW NO. 10; SACCHARIN SODIUM; SODIUM CITRATE; FD&C GREEN NO. 3; SUCRALOSE; SORBITOL; CITRIC ACID MONOHYDRATE; SODIUM BENZOATE

VICKS®DayQuil™ SEVERE HONEY | VICKS®NyQuil™ SEVERE HONEY
COLD & FLU Convenience Pack

VICKS®NyQuil™ SEVERE HONEY

COLD & FLU

Active ingredients (in each 15 mL)

Acetaminophen 325 mg

Dextromethorphan HBr 10 mg

Doxylamine succinate 6.25 mg

Phenylephrine HCl 5 mg

Purpose

Pain reliever/fever reducer

Cough suppressant

Antihistamine

Nasal decongestant

Uses

temporarily relieves common cold/flu symptoms:

- nasal congestion
- sinus congestion & pressure
- cough due to minor throat & bronchial irritation
- cough to help you sleep
- minor aches & pains
- headache
- fever
- sore throat
- runny nose & sneezing
- reduces swelling of nasal passages
- temporarily restores freer breathing through the nose
- promotes nasal and/or sinus drainage

Warnings

Liver warning:

This product contains acetaminophen. Severe liver damage may occur if

- adult takes more than 4 doses (30 mL each) in 24 hours, which is the maximum daily amount for this product
- child takes more than 4 doses (15 mL each) in 24 hours, which is the maximum daily amount for this product
- taken with other drugs containing acetaminophen
- adult has 3 or more alcoholic drinks daily while using this product

Allergy Alert:

Acetaminophen may cause severe skin reactions. Symptoms may include:

- skin reddening
- blisters
- rash

If a skin reaction occurs, stop use and seek medical help right away

Sore throat warning:

If sore throat is severe, persists for more than 2 days, is accompanied or is followed by fever, headache, rash, nausea, or vomiting, consult a doctor promptly.

Do not use

- with any other drug containing acetaminophen (prescription or nonprescription). If you are not sure whether a drug contains acetaminophen, ask a doctor or pharmacist.
- if you are now taking a prescription monoamine oxidase inhibitor (MAOI) (certain drugs for depression, psychiatric or emotional conditions, or Parkinson's disease), or for 2 weeks after stopping the MAOI drug. If you do not know if your prescription drug contains an MAOI, ask a doctor or pharmacist before taking this product.
- to make a child sleepy

Ask a doctor before use if you have

- liver disease
- heart disease
- high blood pressure
- thyroid disease
- diabetes
- glaucoma
- cough that occurs with too much phlegm (mucus)
- a breathing problem or chronic cough that lasts or as occurs with smoking, asthma, chronic bronchitis, or emphysema
- trouble urinating due to enlarged prostate gland

Ask a doctor or pharmacist before use if you are

- taking sedatives or tranquilizers
- taking the blood thinning drug warfarin

When using this product

- do not use more than directed
- excitability may occur, especially in children
- marked drowsiness may occur
- avoid alcoholic drinks
- be careful when driving a motor vehicle or operating machinery
- alcohol, sedatives, and tranquilizers may increase drowsiness

Stop use and ask a doctor if

- you get nervous, dizzy or sleepless
- pain, nasal congestion or cough gets worse or lasts more than 5 days (children) 7 days (adults)
- fever gets worse or lasts more than 3 days
- redness or swelling is present
- new symptoms occur
- cough comes back, or occurs with rash or headache that lasts.

These could be signs of a serious condition.

If pregnant or breast-feeding,

ask a health professional before use.

Keep out of reach of children.

In case of overdose, get medical help or contact a Poison Control Center right away. Quick medical attention is critical for adults as well as for children even if you do not notice any signs or symptoms.

Directions

- take only as directed
- only use the dose cup provided
- do not exceed 4 doses per 24 hrs

adults & children 12 yrs & over | 30 mL every 4 hrs
children 6 to under 12 yrs | 15 mL every 4 hrs
children 4 to under 6 yrs | do not use unless directed by a doctor
children under 4 yrs | do not use

Other information

- each 15 mL contains:sodium 14 mg
- Store at no greater than 25°C and do not refrigerate.

INACTIVE INGREDIENT

citric acid, D&C Yellow No. 10, FD&C Green No. 3, FD&C Red No. 40, FD&C Yellow No. 6, flavor, glycerin, propylene glycol, saccharin sodium, sodium benzoate, sodium citrate, sorbitol, sucralose, water, xanthan gum

Questions?

1-800-362-1683

VICKS®DayQuil™ SEVERE HONEY FLAVOR

COLD & FLU

Active ingredients (in each 15 mL)

Acetaminophen 325 mg

Dextromethorphan HBr 10 mg

Guaifenesin 200 mg

Phenylephrine HCl 5 mg

Purpose

Pain reliever/fever reducer

Cough suppressant

Expectorant

Nasal decongestant

Uses

- temporarily relieves common cold/flu symptoms:
- nasal congestion
- sinus congestion & pressure
- cough due to minor throat & bronchial irritation
- minor aches & pains
- headache
- fever
- sore throat
- reduces swelling of nasal passages
- temporarily restores freer breathing through the nose
- promotes nasal and/or sinus drainage
- helps loosen phlegm (mucus) and thin bronchial secretions to rid the bronchial passageways of bothersome mucus and make coughs more productive.

Warnings

Liver warning:

This product contains acetaminophen. Severe liver damage may occur if

- adult takes more than 4 doses (30 mL each) in 24 hours, which is the maximum daily amount for this product
- child takes more than 4 doses (15 mL each) in 24 hours, which is the maximum daily amount for this product
- taken with other drugs containing acetaminophen
- adult has 3 or more alcoholic drinks daily while using this product

Allergy Alert:

Acetaminophen may cause severe skin reactions. Symptoms may include:

- skin reddening
- blisters
- rash

If a skin reaction occurs, stop use and seek medical help right away

Sore throat warning:

If sore throat is severe, persists for more than 2 days, is accompanied or is followed by fever, headache, rash, nausea, or vomiting, consult a doctor promptly.

Do not use

- with any other drug containing acetaminophen (prescription or nonprescription). If you are not sure whether a drug contains acetaminophen, ask a doctor or pharmacist.
- if you are now taking a prescription monoamine oxidase inhibitor (MAOI) (certain drugs for depression, psychiatric or emotional conditions, or Parkinson's disease), or for 2 weeks after stopping the MAOI drug. If you do not know if your prescription drug contains an MAOI, ask a doctor or pharmacist before taking this product.

Ask a doctor before use if you have

- liver disease
- heart disease
- high blood pressure
- thyroid disease
- diabetes
- trouble urinating due to enlarged prostate gland
- cough that occurs with too much phlegm (mucus)
- persistent or chronic cough such as occurs with smoking, asthma, chronic bronchitis, or emphysema

Ask a doctor or pharmacist before use if you are

taking the blood thinning drug warfarin

When using this product,

do not use more than directed

Stop use and ask a doctor if

- you get nervous, dizzy or sleepless
- pain, nasal congestion or cough gets worse or lasts more than 5 days (children) 7 days (adults)
- fever gets worse or lasts more than 3 days
- redness or swelling is present
- new symptoms occur
- cough comes back, or occurs with rash or headache that lasts.

These could be signs of a serious condition.

If pregnant or breast-feeding,

ask a health professional before use.

Keep out of reach of children.

In case of overdose, get medical help or contact a Poison Control Center right away. Quick medical attention is critical for adults as well as for children even if you do not notice any signs or symptoms.

Directions

- take only as directed
- only use the dose cup provided
- do not exceed 4 doses per 24 hrs

adults & children 12 yrs & over | 30 mL every 4 hrs
children 6 to under 12 yrs | 15 mL every 4 hrs
children 4 to under 6 yrs | ask a doctor
children under 4 yrs | do not use

Other information

- each 15 mL contains: sodium 14 mg
- Store at no greater than 25°C and do not refrigerate

Inactive ingredients

citric acid, D&C Yellow No. 10, FD&C Green No. 3, FD&C Red No. 40, FD&C Yellow No. 6, flavor, glycerin, propylene glycol, saccharin sodium, sodium benzoate, sodium citrate, sorbitol, sucralose, water, xanthan gum

Questions?

1-800-362-1683

TAMPER EVIDENT:Do not use if printed shrinkband seal around the neck is broken or missing.

Made in Canada

DIST. BY PROCTER & GAMBLE,

CINCINNATI, OH 45202

VICKS®DayQuil™ SEVERE HONEY | VICKS®NyQuil™ SEVERE HONEY COLD & FLU Convenience Pack

FLAVORED WITH REAL HONEY
DAY & NIGHT PACK
Vicks®
DayQuil™ Severe Honey Cold & Flu
Acetaminophen, Dextromethorphan HBr, Guaifenesin, Phenylephrine HCl
Headache, Fever, Sore Throat, Minor Aches & Pains
Chest Congestion, Thins & Lons Mucus
Nasal Congestion, Sinus Pressure
Cough
Non-Drowsy
NyQuil™ Severe Honey Cold & Flu
Acetaminophen, Dextromethorphan HBr, Doxylamine succinate, Phenylephrine HCl
Headache, Fever, Sore Throat, Minor Aches & Pains
Nasal Congestion, Sinus Pressure
Sneezing, Runny Nose
Cough
Nighttime Relief
2 Bottles - 1 Dayquil/1 NYQUIL 12 FL OZ (354 mL) EACH; TOTAL 24 FL OZ (708 mL)